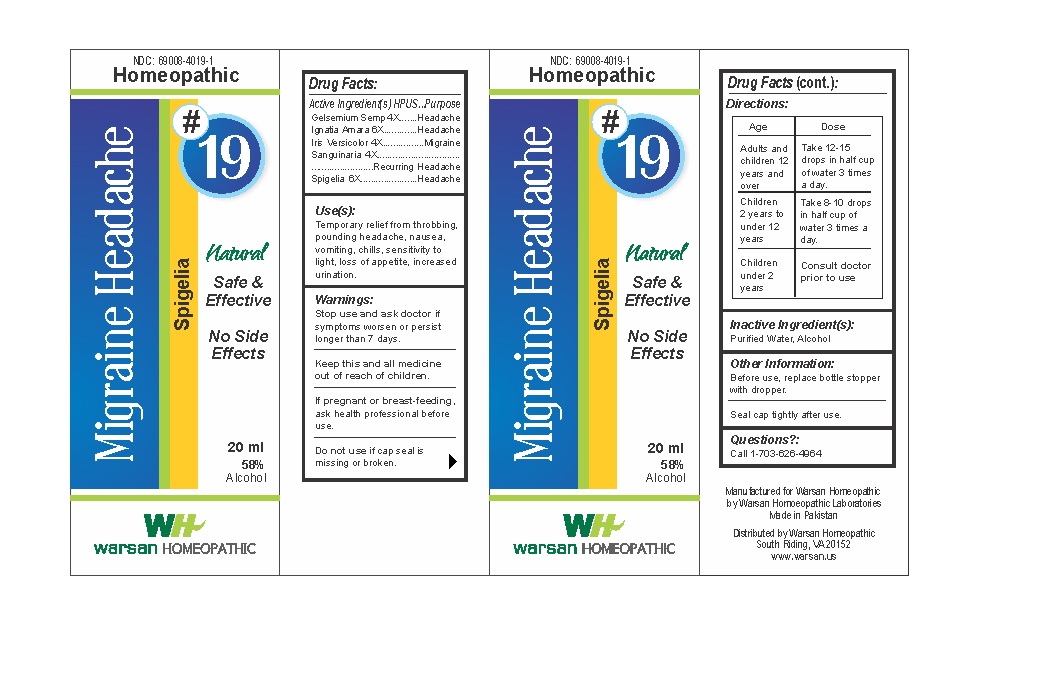 DRUG LABEL: Combination Remedy 19 - Migraine Headache
NDC: 69008-4019 | Form: SOLUTION/ DROPS
Manufacturer: Warsan Homoeopathic Laboratories
Category: homeopathic | Type: HUMAN OTC DRUG LABEL
Date: 20171225

ACTIVE INGREDIENTS: IRIS VERSICOLOR ROOT 4 [hp_X]/1 mL; SANGUINARIA CANADENSIS ROOT 4 [hp_X]/1 mL; GELSEMIUM SEMPERVIRENS ROOT 4 [hp_X]/1 mL; STRYCHNOS IGNATII SEED 6 [hp_X]/1 mL; SPIGELIA MARILANDICA ROOT 6 [hp_X]/1 mL
INACTIVE INGREDIENTS: ALCOHOL; WATER

Stop use and ask doctor if symptoms worsen or persist longer than 7 days.

If pregnant or breast-feeding, ask health professional before use.

Do not use if tamper evident seal is missing or broken.

Keep out of reach of children.

ACTIVE INGREDIENT

Gelsemium Semp 4X

Ignatia Amara 6X

Iris Versicolor 4X

Sanguinaria 4X

Spigelia 6X

PURPOSE

Temporary relief from throbbing, pounding headache, nausea, vomiting, chills, sensitivity to light, loss of appetite, increased urination.

INACTIVE INGREDIENT

Purified Water

Alcohol

DOSAGE AND ADMINISTRATION

Adults and children 12 years and older: Take 10-15 drops in half cup of water 3 times a day.

Children 2 years to under 12 years: Take 8-10 drops in half cup of water of 3 times a day.

Children under 2 years: Consult doctor prior to use.

INDICATIONS AND USAGE

Temporary relief from throbbing, pounding headache, nausea, vomiting, chills, sensitivity to light, loss of appetite, increased urination.